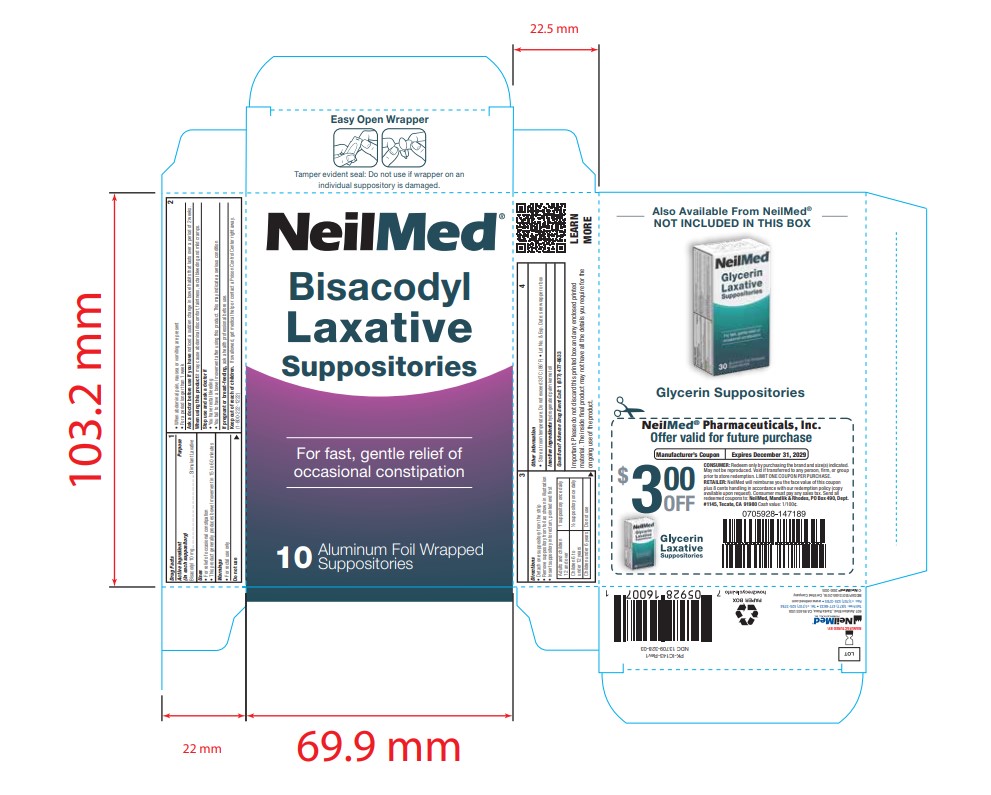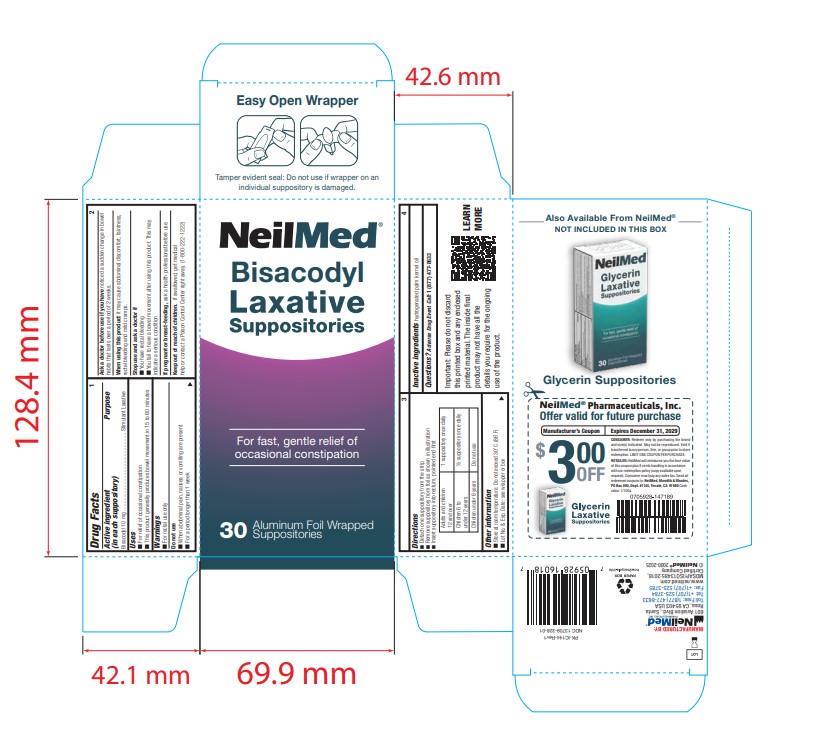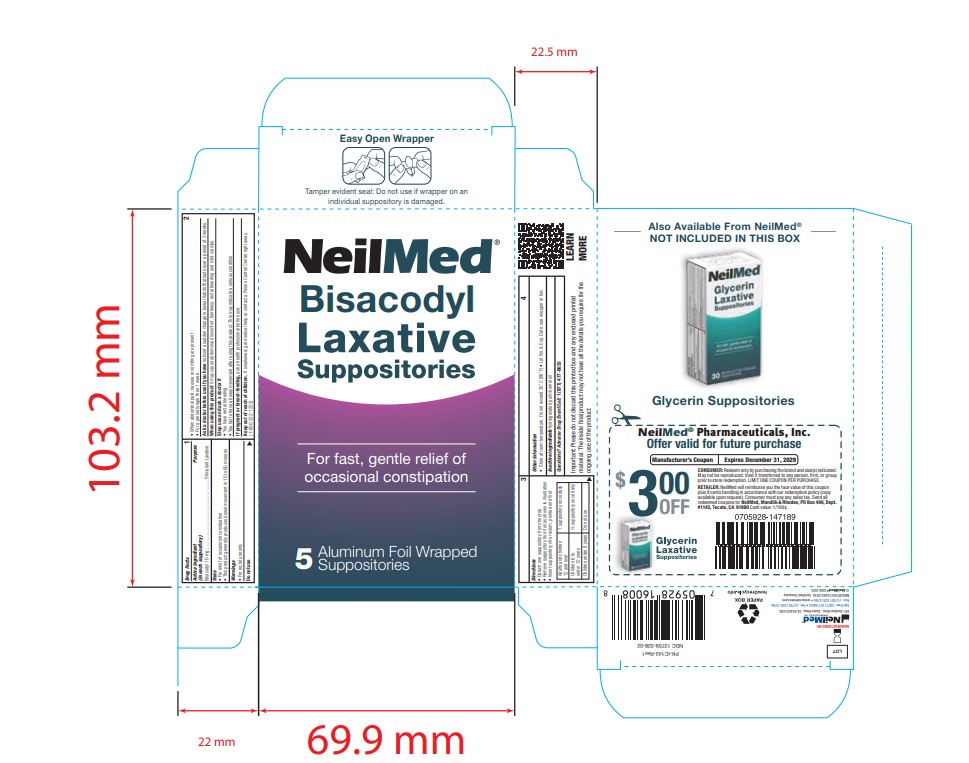 DRUG LABEL: Bisacodyl Laxative
NDC: 13709-328 | Form: SUPPOSITORY
Manufacturer: Neilmed Pharmaceuticals Inc.
Category: otc | Type: HUMAN OTC DRUG LABEL
Date: 20250703

ACTIVE INGREDIENTS: BISACODYL 10 mg/1.8 g
INACTIVE INGREDIENTS: HYDROGENATED PALM KERNEL OIL

Bisacodyl LaxativeAluminium Foil wrapped Suppositories

Drug Facts: Active Ingredient

(in each suppository)
Bisacodyl 10 mg

Uses

- for relief of occasional constipation
- this product generally produces bowel movement in 15 to 60 minutes

Warnings

- For rectal use only

Do not use

- when abdominal pain, nausea or vomiting are present
- for a period longer than 1 week

Ask a doctor before use

if you have noticed a sudden change in bowel habits that lasts over a period of 2 weeks

When using this product

it may cause abdominal discomfort, faintness, rectal bleeding and mild cramps

Stop use and ask a doctor if

- you have rectal bleeding
- you fail to have a bowel movement after using this product. This may indicate a serious condition

If pregnant or breast-feeding,

ask a health professional before use.

Keep out of reach of children.

If swallowed, get medical help or contact a Poison Control Center right away. (1-800-222-1222)

Directions

- Detach one suppository from the strip
- Remove suppository from foil as shown in illustration
- Insert suppository into rectum, pointed end first

Adults and children 12 and over | 1 suppository once daily
Children 6 to under 12 years | 1/2 suppository daily
Children under 6 years | Do not use

Other Information

- Store at room temperature. Do not exceed 30˚ C (86˚ F)
- Lot No. & Exp. Date: see wrapper or box

Inactive Ingredients

hydrogenated palm kernel oil

Questions?

Adverse Drug Event Call: 1(877) 477-8633

Important:

Please do not discard this printed box and any enclosed printed material. The inside final product may not have all the details you require for the ongoing use of the product.

Purpose

Purpose - Vasoconstrictor